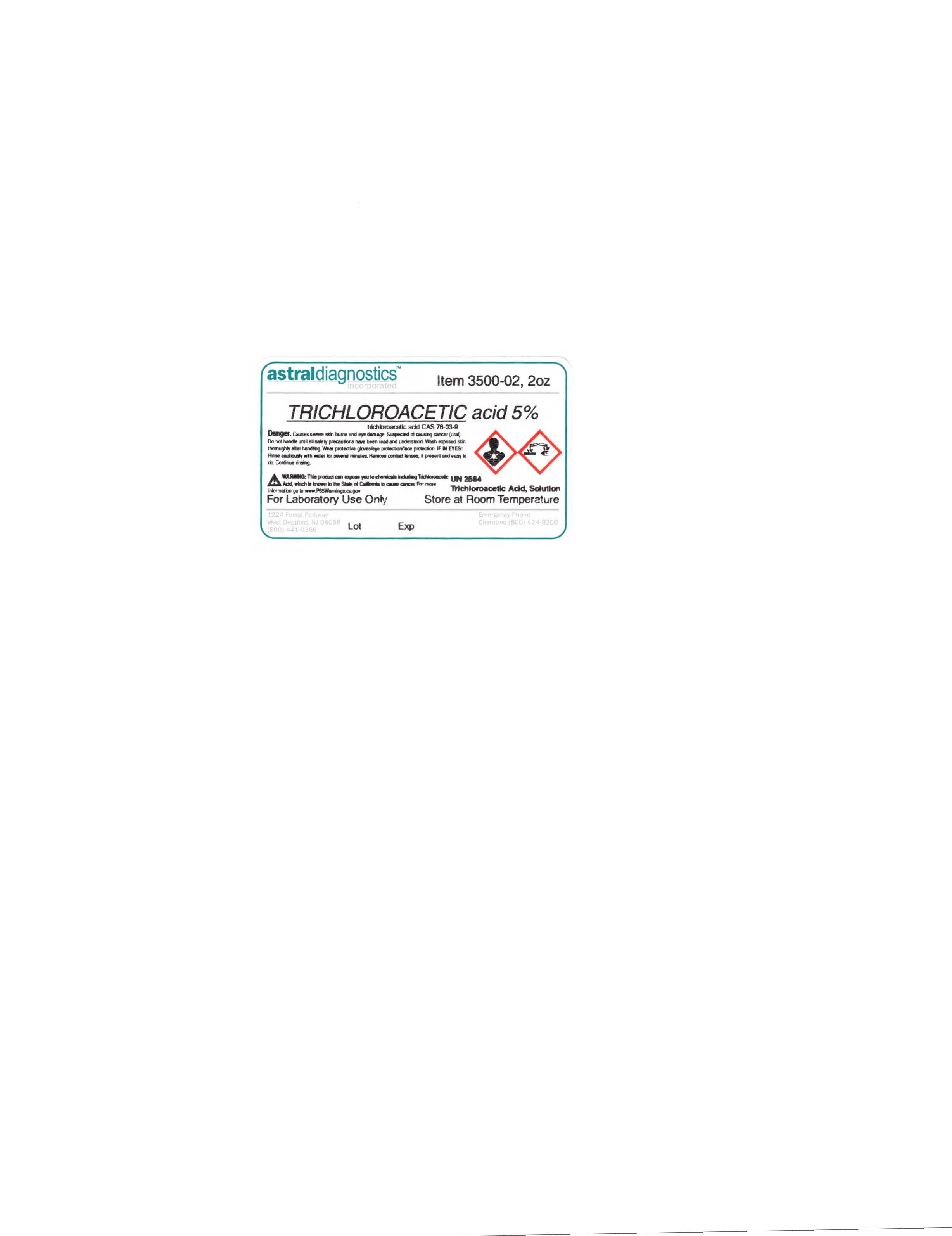 DRUG LABEL: Trichloroacetic Acid 5%
NDC: 72272-001 | Form: LIQUID
Manufacturer: Astral Diagnostics Inc
Category: prescription | Type: HUMAN PRESCRIPTION DRUG LABEL
Date: 20201221

ACTIVE INGREDIENTS: TRICHLOROACETIC ACID 5 g/100 mL

Trichloroacetic Acid